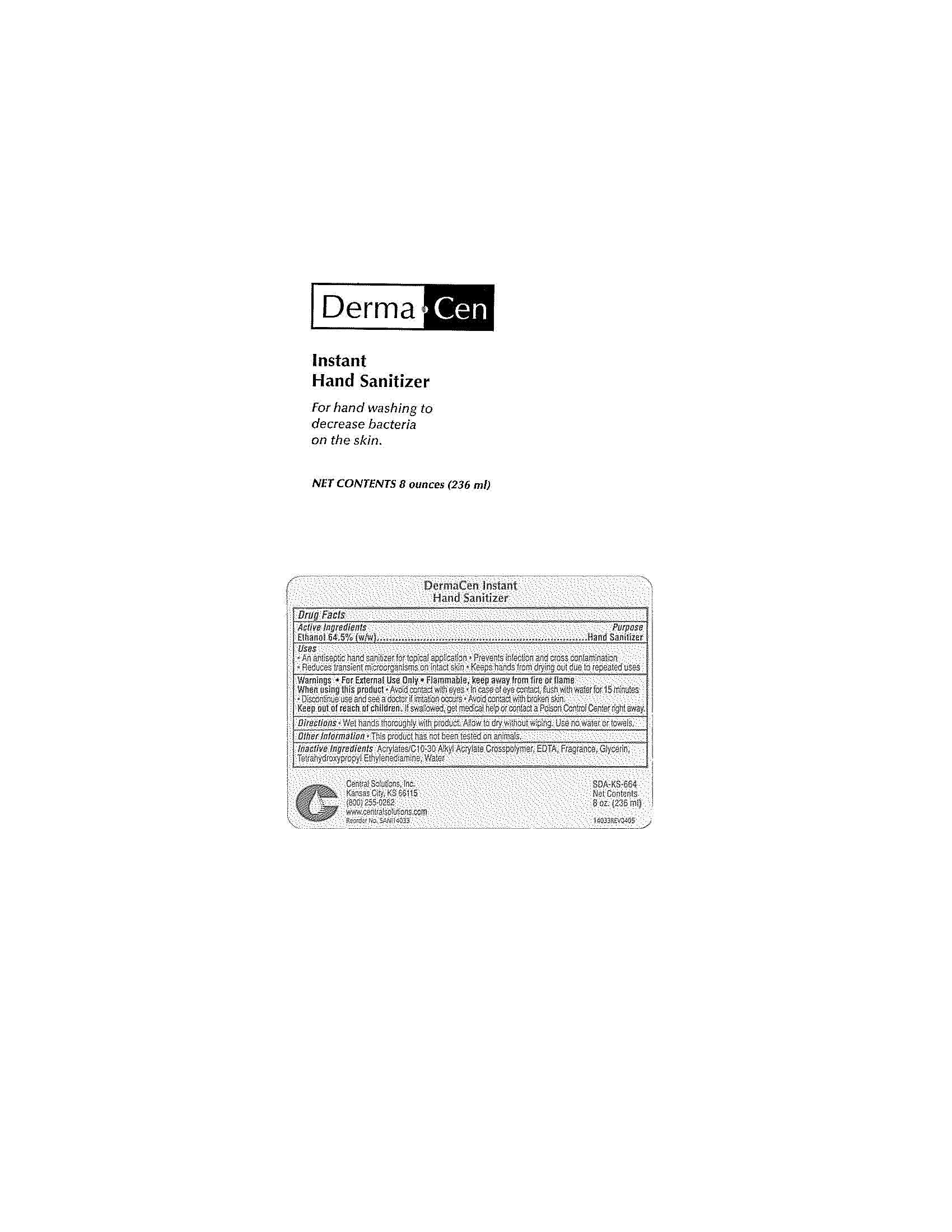 DRUG LABEL: DermaCen Instant Hand Sanitizer
NDC: 62654-140 | Form: LIQUID
Manufacturer: Central Solutions Inc
Category: otc | Type: HUMAN OTC DRUG LABEL
Date: 20241209

ACTIVE INGREDIENTS: ALCOHOL 64.5 mL/100 mL
INACTIVE INGREDIENTS: CARBOMER INTERPOLYMER TYPE A (ALLYL SUCROSE CROSSLINKED); EDETIC ACID; GLYCERIN; WATER

Drug Facts 62654-140

Active Ingredients

Ethanol 64.5% (w/w)

Purpose

Hand Sanitizer

Uses

An antiseptic hand sanitizer for topical application

Prevents infection and cross contamination

Reduces transient microorganisms on intact skin

Keep hands from drying due to repeated uses

Warnings

For External Use Only

Flammable, keep away from fire or flame

When using this product

Avoid contact with eyes

In case of eye contact, flush with water for 15 minutes

Discontinue use and see a doctor if irritation occurs

Avoid contact with broken skin

Keep out of reach of children.

If swallowed, get medical help or contact a Poison Control Center right away.

Directions

Wet hands thoroughly with product.

Allow to dry without wiping.

Use no water or towels.

Other Information

This product has not been tested on animals.

Inactive Ingredients

Acrylates/C10-30 Alkyl Acrylate Crosspolymer, EDTA, Fragrance, Glycerin, Tetrahydroxypropyl Ethylenediamine, Water

PACKAGE LABEL

DermaCen

Instant

Hand Sanitizer

For hand washing to decrease bacteria on the skin.

Net Contents 8 ounces (236 ml)